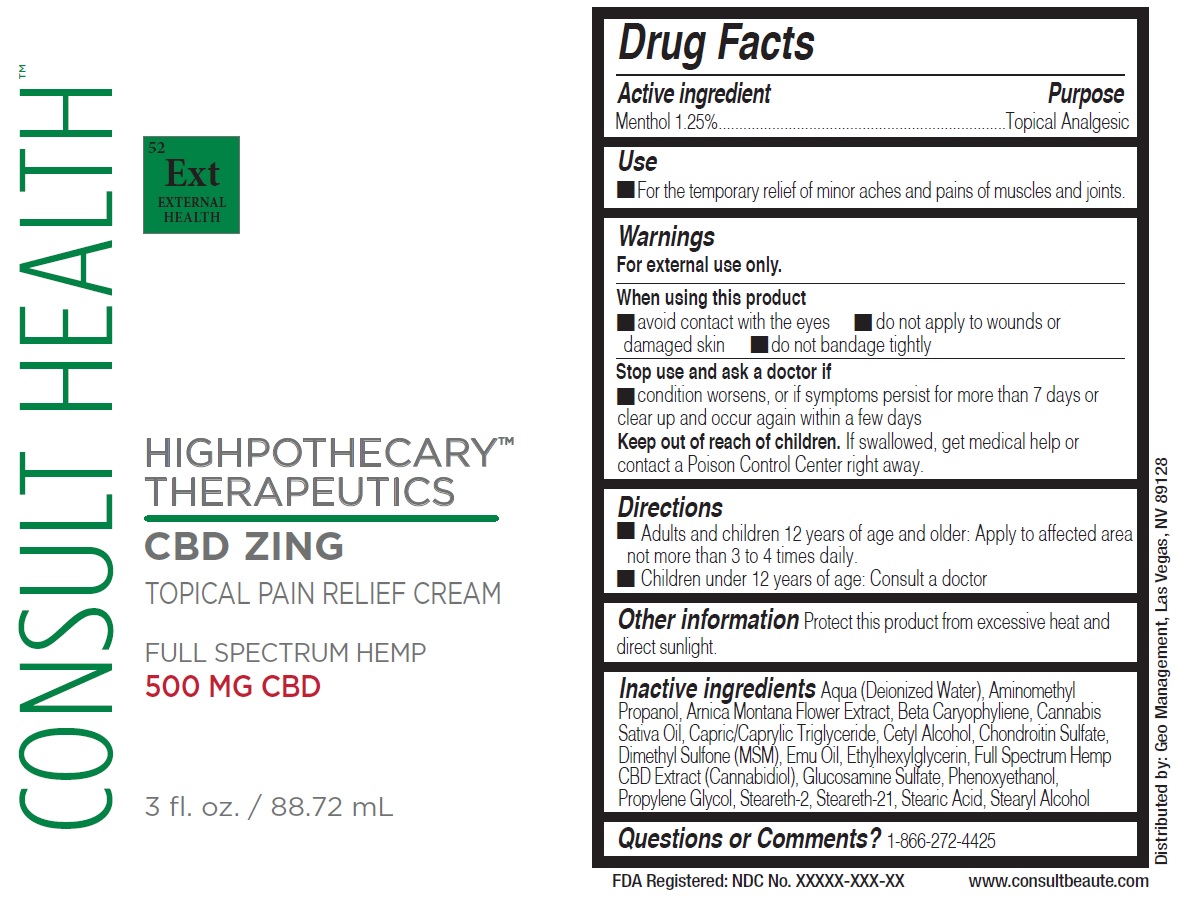 DRUG LABEL: Highpothecary Therapeutics CBD Zing
NDC: 70803-001 | Form: CREAM
Manufacturer: SIBORG LLC
Category: otc | Type: HUMAN OTC DRUG LABEL
Date: 20210723

ACTIVE INGREDIENTS: MENTHOL 12.5 mg/1 mL
INACTIVE INGREDIENTS: WATER; AMINOMETHYLPROPANOL; ARNICA MONTANA FLOWER; CETYL ALCOHOL; DIMETHYL SULFONE; EMU OIL; ETHYLHEXYLGLYCERIN; CANNABIDIOL; GLUCOSAMINE SULFATE; PHENOXYETHANOL; PROPYLENE GLYCOL; STEARETH-2; STEARETH-21; STEARIC ACID; STEARYL ALCOHOL

Highpothecary Therapeutics CBD Zing

Active ingredient

Menthol 1.25%

Purpose

Topical Analgesic

Use

- For the temporary relief of minor aches and pains of muscles and joints.

Warnings

For external use only.

When using this product

- avoid contact with the ey es
- do not apply to wounds or damaged skin
- do not bandage tightly

Stop use and ask a doctor if

- condition worsens, or if symptoms persist for more than 7 days or clear up and occur again within a few days

Keep out of reach of children.

If swallowed, get medical help or contact a Poison Control Center right away.

Directions

- Adults and children 12 years of age and older: Apply to affected area not more than 3 to 4 times daily.
- Children under 12 years of ag e: Consult a doctor

Other information

Protect this product from excessive heat and direct sunlight.

Inactive ingredients

Aqua (Deionized Water), Aminomethyl Propanol, Arnica Montana Flower Extract, Beta Caryophyliene, Cannabis Sativa Oil, Capric/Caprylic Triglyceride, Cetyl Alcohol, Chondroitin Sulfate, Dimethyl Sulfone (MSM), Emu Oil, Ethylhexylglycerin, Full Spectrum Hemp CBD Extract (Cannabidiol), Glucosamine Sulfate, Phenoxyethanol, Propylene Glycol, Steareth-2, Steareth-21, Stearic Acid, Stearyl Alcohol

Questions or Comments?

1-866-272-4425